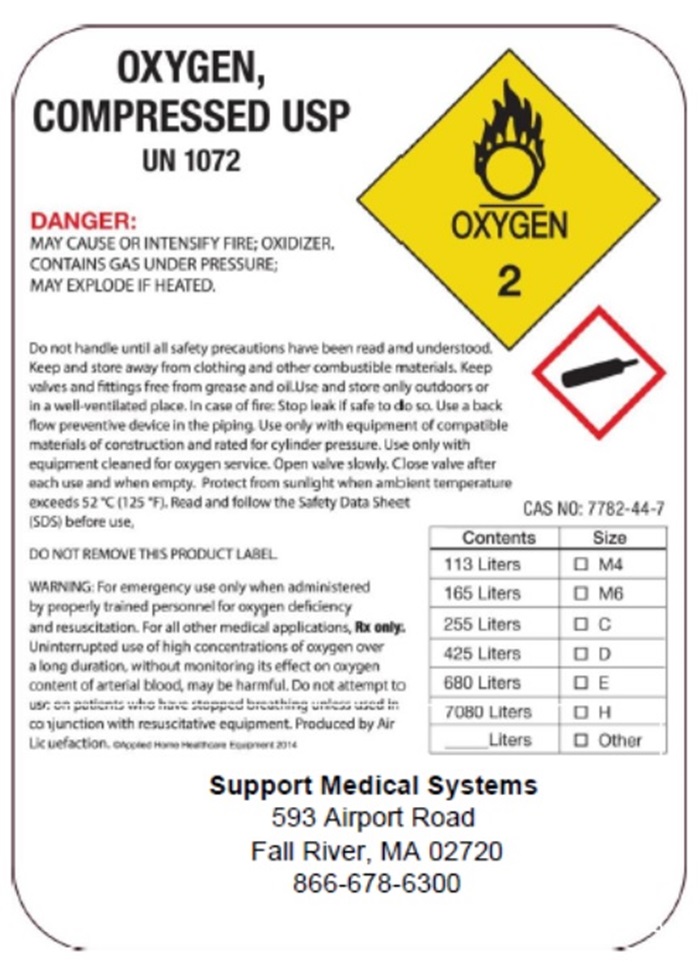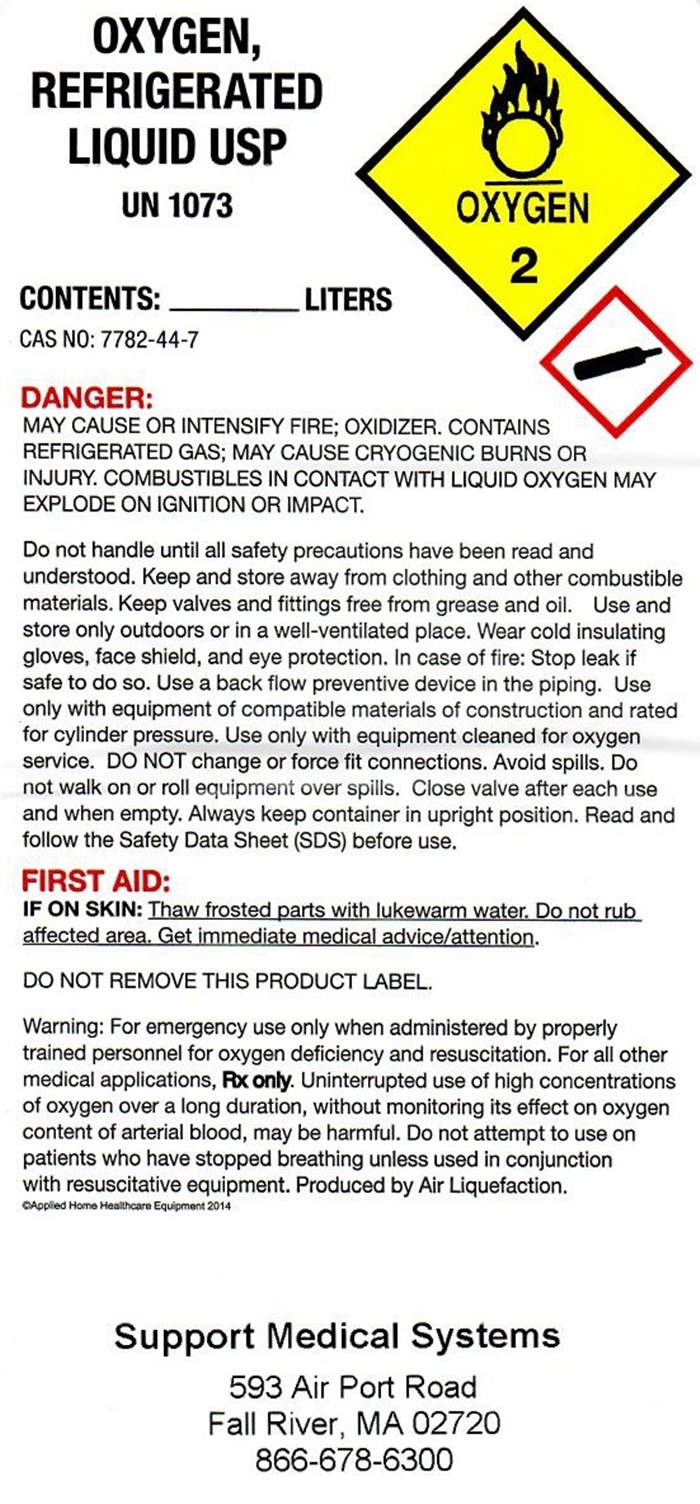 DRUG LABEL: Oxygen
NDC: 76091-002 | Form: GAS
Manufacturer: Support Medical Systems, Inc.
Category: prescription | Type: HUMAN PRESCRIPTION DRUG LABEL
Date: 20241028

ACTIVE INGREDIENTS: OXYGEN 99 L/100 L

Oxygen

Oxygen Label

OXYGEN, COMPRESSED USP UN1072 OXYGEN 2

DANGER: MAY CAUSE OR INTENSIFY FIRE; OXIDIZER, CONTAINS GAS UNDER PRESSURE; MAY EXPLODE IF HEATED.

Do not handle until all safety precautions have been read and understood. Keep and store away from clothing and other combustive material. Keep valves and fittings free from grease and oil. Use and store only outdoors or in a well-ventilated place. In case of fire: Stop leak if safe to do so. Use a back flow preventive device in the piping. Use only with equipment of compatible materials of construction and rated for cylinder pressure. Use only with equipment cleaned for oxygen service. Open valve slowly. Close valve after each use and when empty. Protect from sunlight when ambient temperature exceeds 52° C (125° F). Read and follow the Safety Data Sheet (SDS) before use.

DO NOT REMOVE THIS PRODUCT LABEL

WARNING: For emergency use only when administered by properly trained personnel for oxygen deficiency and resuscitation. For all other medical applications. Rx only. Uninterrupted use of high concentrations of oxygen over a long duration without monitoring its effect on oxygen content of arterial blood, may be harmful. Do not attempt to use on patients who have stopped breathing unless used in conjunction with resuscitative equipment. Produced by Air Liquefaction. © Applied Home Healthcare Equipment 2014

CAS 7782-44-7

Contents Size

113 Liters __M4

165 Liters __M6

255 Liters __ C

425 Liters __ D

680 Liters __ E

7080 Liters __ H

___ Liters __ Other

Support Medical Systems

593 Airport Road

Fall River, MA 02720

866-678-6300

Refrigerated Oxygen

OXYGEN, REFRIGERATED LIQUID USP

UN1073 OXYGEN 2

CONTENTS: __________________ LITERS.

CAS NO: 7782-44-7

DANGER:

MAY CAUSE OR INTENSIFY FIRE; OXIDIZER CONTAINS REFRRIGERATED GAS; MAY CAUSE CRYOGENIC BURNS OR INJURY, COMBUSTIBLES IN CONTACT WITH LIQUID OXYGEN MAY EXPLODE ON IGNITION OR IMPACT.

Do not handle until all safety precautions have been read and understood. Keep and store away from clothing and other combustible materials. Keep valves and fittings free from grease and oil. Use and store only outdoors or in a well-ventilated place. Wear cold insulating gloves, face shield, and eye protection. In case of fire: Stop leak if safe to do so. Use a back flow preventive device in the piping. Use only the equipment of compatible materials equipment cleaned for oxygen service. DO NOT change or force fit connections. Avoid spills. Do not walk on or roll equipment over spills. Close valve after each use and when empty. Always keep container in upright position. Read and follow the Safety Data Sheet (SDS) before use.

FIRST AID:

IF ON SKIN: Thaw affected parts with lukewarm water. Do not rub affected area. Get immediate medical advice/attention.

DO NOT REMOVE THIS PRODUCT LABEL.

WARNING: For emergency use only when administered by properly trained personnel for oxygen deficiency and resuscitation. For all other medical applications, Rx only. Uninterrupted use of high concentrations of oxygen over a long duration, without monitoring its effect on oxygen content of arterial blood, may be harmful. Do not attempt to use on patients who have stopped breathing unless used in conjunction of resuscitative equipment. Use a back flow preventive device in the piping. Cylinder temperature should not exceed 52°C (125°F). PRODUCED BY AIR LIQUEFACTION

Support Medical Systems

593 Airport Road

Fall River, MA 02720

866-678-6300